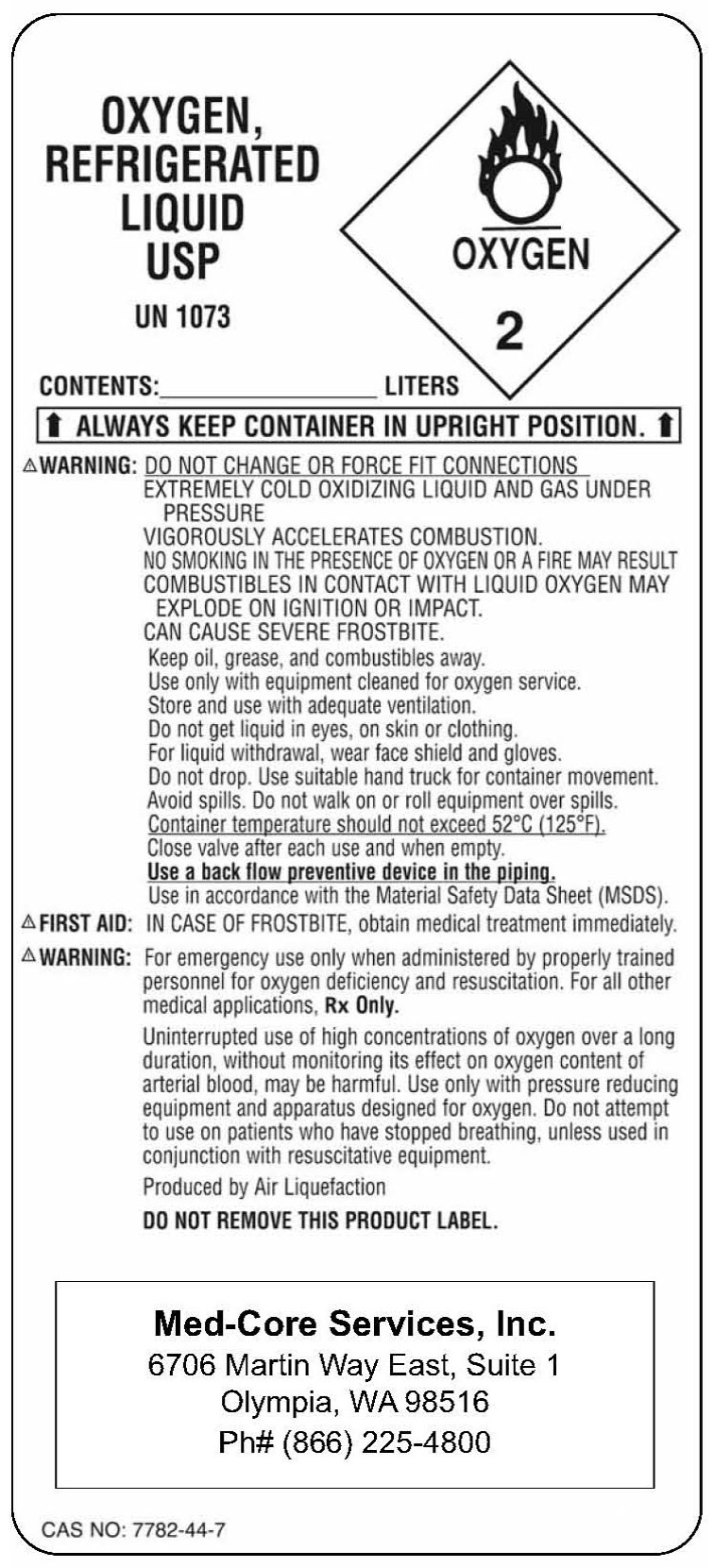 DRUG LABEL: Oxygen
NDC: 67491-7777 | Form: GAS
Manufacturer: Med-Core Services, Inc.
Category: prescription | Type: HUMAN PRESCRIPTION DRUG LABEL
Date: 20091230

ACTIVE INGREDIENTS: Oxygen 99 L/100 L

Oxygen